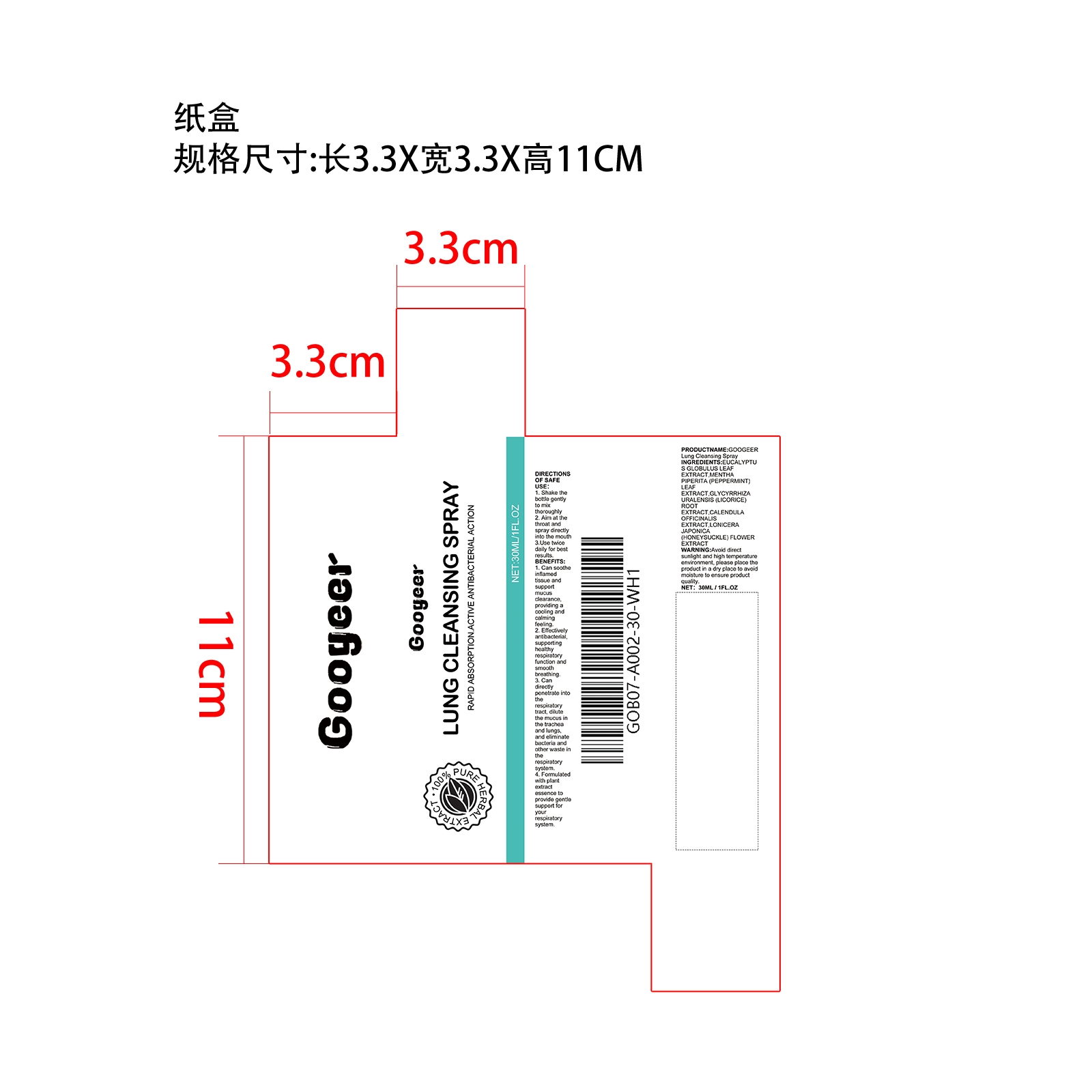 DRUG LABEL: Liquid
NDC: 84067-849 | Form: LIQUID
Manufacturer: Shantou Youjia E-Commerce Co.,Ltd.
Category: otc | Type: HUMAN OTC DRUG LABEL
Date: 20240408

ACTIVE INGREDIENTS: EUCALYPTUS GLOBULUS LEAF 3 mg/30 mg
INACTIVE INGREDIENTS: CALENDULA OFFICINALIS WHOLE 6 mg/30 mg; GLYCYRRHIZA URALENSIS ROOT 7.5 mg/30 mg; MENTHA PIPERITA LEAF 4.5 mg/30 mg; LONICERA JAPONICA FLOWER 9 mg/30 mg

GOOGEER Lung Cleansing Spray